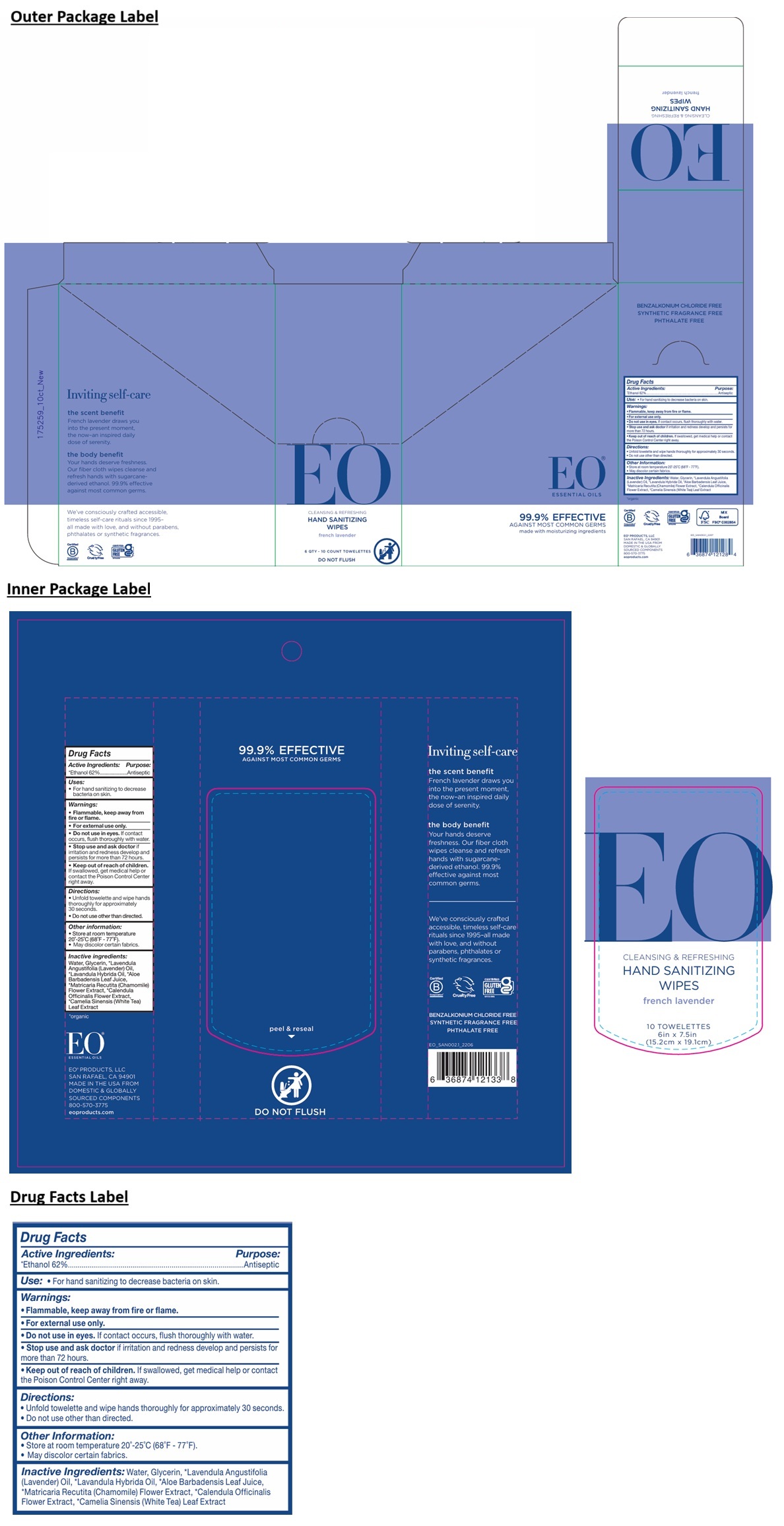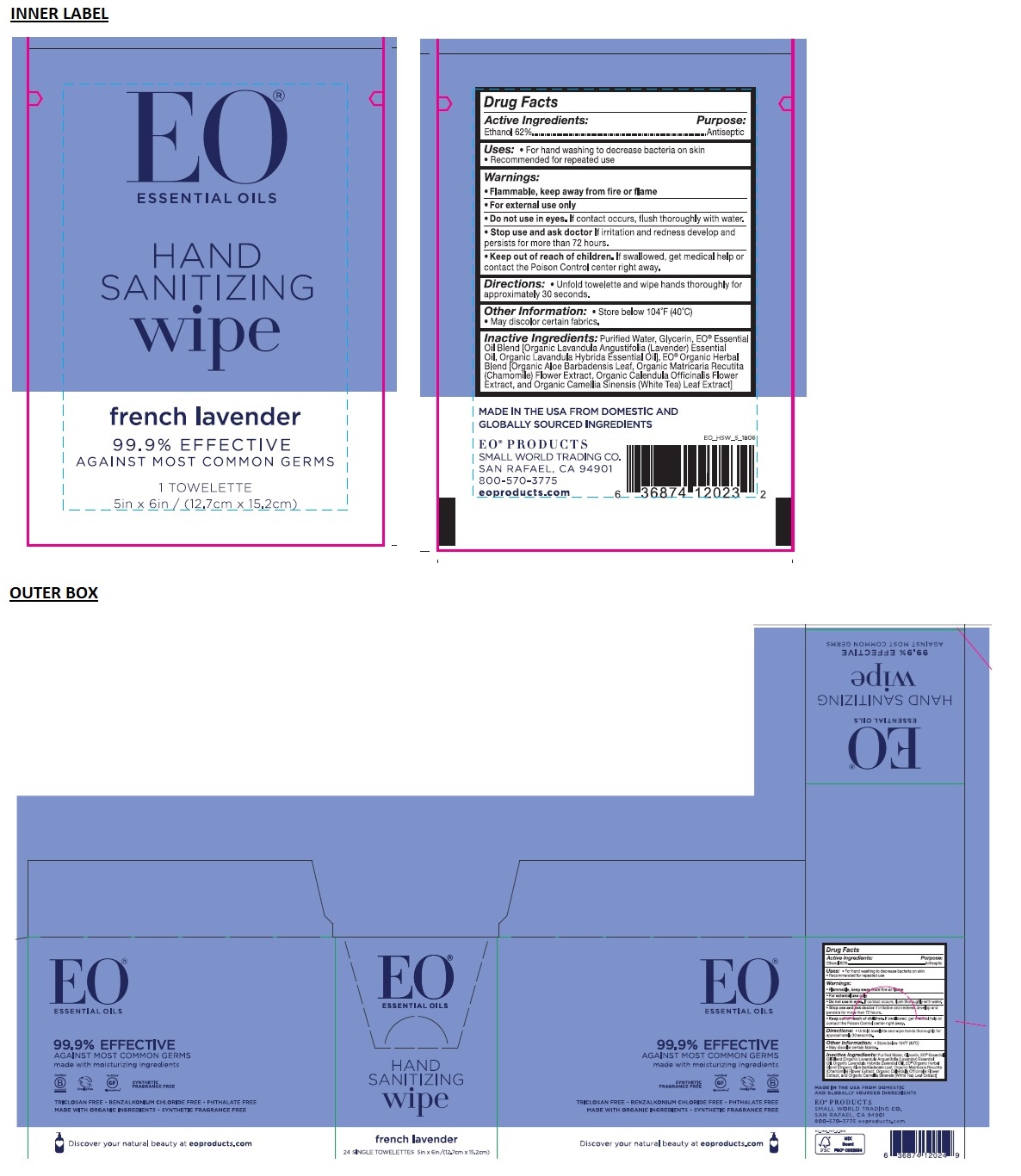 DRUG LABEL: EO Hand Sanitizer Wipes Lavender
NDC: 54748-502 | Form: CLOTH
Manufacturer: EO Products, LLC
Category: otc | Type: HUMAN OTC DRUG LABEL
Date: 20251127

ACTIVE INGREDIENTS: ALCOHOL 62 mL/100 mL
INACTIVE INGREDIENTS: WATER; GLYCERIN; LAVENDER OIL; LAVANDIN OIL; ALOE VERA LEAF JUICE; CHAMOMILE; CALENDULA OFFICINALIS FLOWER; WHITE TEA

EO® HAND SANITIZING WIPES french lavender

Active Ingredients:

*Ethanol 62%

Purpose:

Antiseptic

Use:

- For hand sanitizing to decrease bacteria on skin.

Warnings:

- Flammable, keep away from fire or flame.
- For external use only.
- Do not use in eyes. If contact occurs, flush thoroughly with water.
- Stop use and ask a doctor if irritation and redness develop and persists for more than 72 hours.

- Keep out of reach of children. If swallowed, get medical help or contact the Poison Control Center right away.

Directions:

- Unfold towelette and wipe hands thoroughly for approximately 30 seconds.
- Do not use other than directed.

Other information:

- Store at room temperature 20°-25°C (68°F - 77°F).
- May discolor certain fabrics.

Inactive Ingredients:

Water, Glycerin, *Lavandula Angustifolia (Lavender) Oil, *Lavandula Hybrida Oil, *Aloe Barbadensis Leaf Juice, *Matricaria Recutita (Chamomile) Flower Extract, *Calendula Officinalis Flower Extract, *Camellia Sinensis (White Tea) Leaf Extract

*organic

CLEANSING & REFRESHING

DO NOT FLUSH

EO® ESSENTIAL OILS

99.9 % EFFECTIVE AGAINST MOST COMMON GERMS
made with moisturizing ingredients

BENZALKONIUM CHLORIDE FREE
SYNTHETIC FRAGRANCE FREE
PHTHALATE FREE

Cruelty Free

CERTIFIED GLUTEN FREE

EO® PRODUCTS, LLC
SAN RAFAEL, CA 94901
MADE IN THE USA FROM DOMESTIC & GLOBALLY SOURCED COMPONENTS
800-570-3775
eoproducts.com

Inviting self-care

the scent benefit
French lavender draws you into the present moment, the now-an inspired daily dose of serenity.

the body benefit
Your hands deserve freshness. Out fiber cloth wipes cleanse and refresh hands with sugarcane-derived ethanol. 99.9% effective against most common germs.

We've consciously crafted accessible, timeless self-care rituals since 1995-all made with love, and without parabens, phthalates or synthetic fragrances.